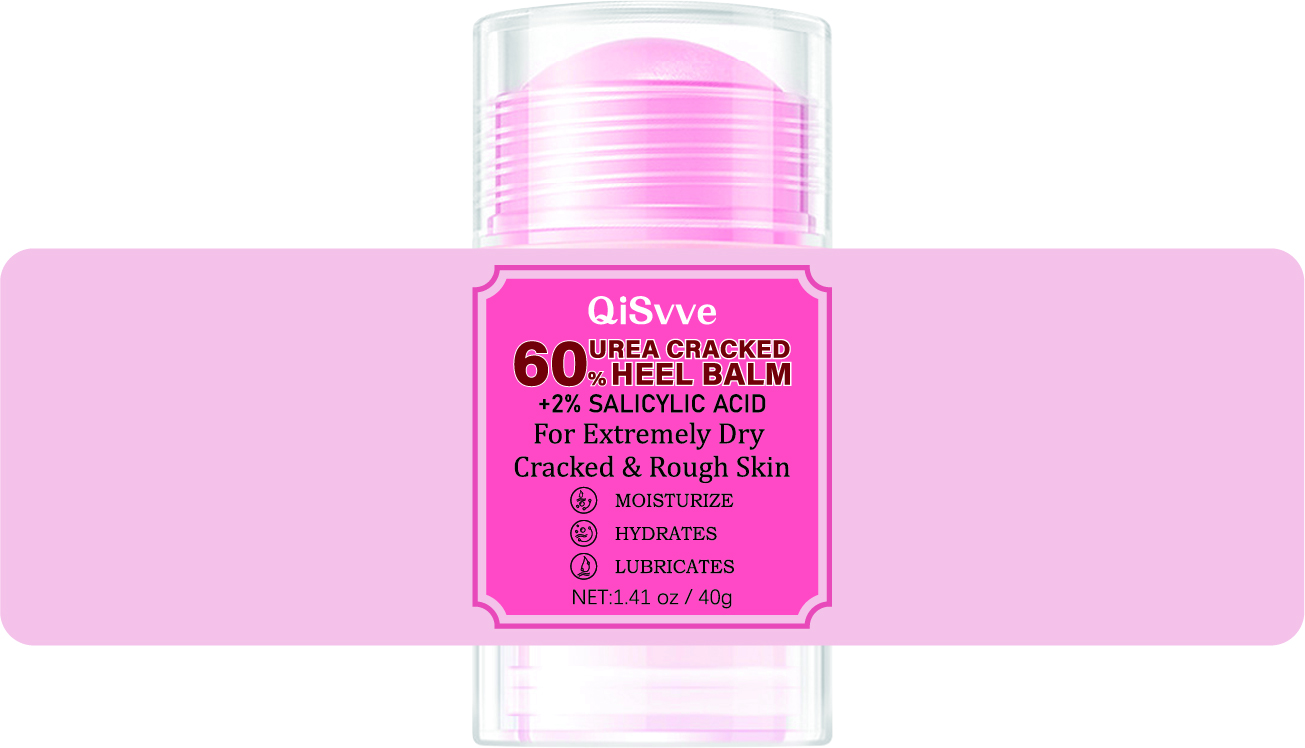 DRUG LABEL: HEEL BALM
NDC: 84117-018 | Form: CREAM
Manufacturer: Shenzhen Hengkaifeng Commerce and Trade Co., Ltd
Category: otc | Type: HUMAN OTC DRUG LABEL
Date: 20240807

ACTIVE INGREDIENTS: UREA 60 g/100 g
INACTIVE INGREDIENTS: WATER; SALICYLIC ACID; MINERAL OIL; PETROLATUM

ACTIVE INGREDIENT

Urea

Purpose

Moisturizing

Use

Keep skin hydrated

Warnings

Please keep it out of the reach of children

When Using

Stay away from the wound

Keep Out Of Reach Of Children

Directions Of Safe Use:

Stay away from the injured area

Inactive ingredients

Water